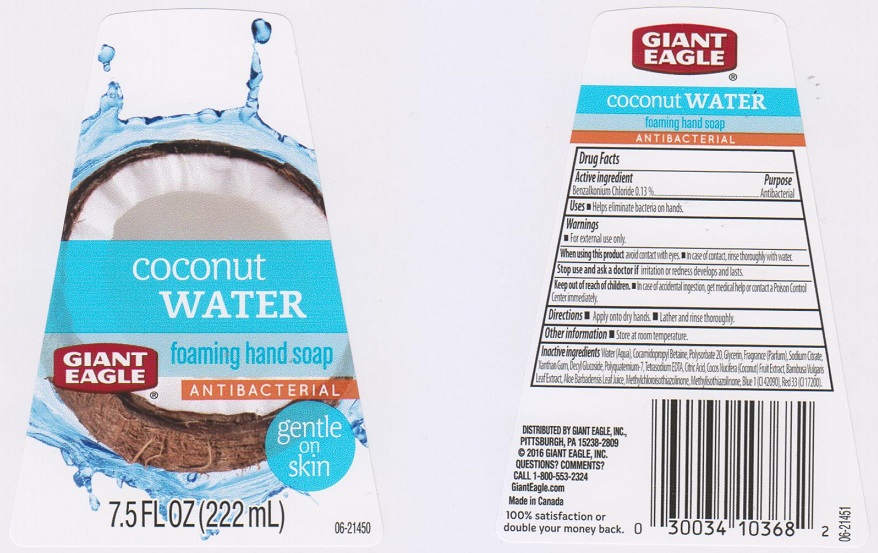 DRUG LABEL: Giant Eagle Coconut Water Foaming
NDC: 63148-842 | Form: LIQUID
Manufacturer: Apollo Health and Beauty Care
Category: otc | Type: HUMAN OTC DRUG LABEL
Date: 20161104

ACTIVE INGREDIENTS: BENZALKONIUM CHLORIDE 1.3 mg/1 mL
INACTIVE INGREDIENTS: WATER; COCAMIDOPROPYL BETAINE; POLYSORBATE 20; GLYCERIN; SODIUM CITRATE; XANTHAN GUM; DECYL GLUCOSIDE; POLYQUATERNIUM-7 (70/30 ACRYLAMIDE/DADMAC; 1600000 MW); EDETATE SODIUM; COCONUT; BAMBUSA VULGARIS LEAF; ALOE VERA LEAF; METHYLCHLOROISOTHIAZOLINONE; METHYLISOTHIAZOLINONE; FD&C BLUE NO. 1; D&C RED NO. 33

Drug Facts

Active ingredient

Benzalkonium chloride 0.13%

Purpose

Antibacterial

Uses

Helps eliminate bacteria on hands.

Warnings

For external use only

When using this product

avoid contact with eyes. In case of contact, rinse thoroughly with water.

Stop use and ask a doctor if

irritation or redness develops and lasts.

Keep out of reach of children.

In case of accidental ingestion, get medical help or contact a Poison Control Center immediately.

Directions

- Apply onto dry hands.
- Lather and rinse thoroughly.

Other information

Store at room temperature.

Inactive ingredients

Water (Aqua), Cocamidopropyl Betaine, Polysorbate 20, Glycerin, Fragrance (Parfum), Sodium Citrate, Xanthan Gum, Decyl Glucoside, Polyquaternium-7, Tetrasodium EDTA, Citric Acid, Cocos Nucifera (Coconut) Fruit Extract, Bambusa Vulgaris Leaf Extract, Aloe Barbadensis Leaf Juice, Methychloroisothiazolinone, Methylisothiazolinone, Blue 1 (CI 42090), Red 33 (CI 17200).